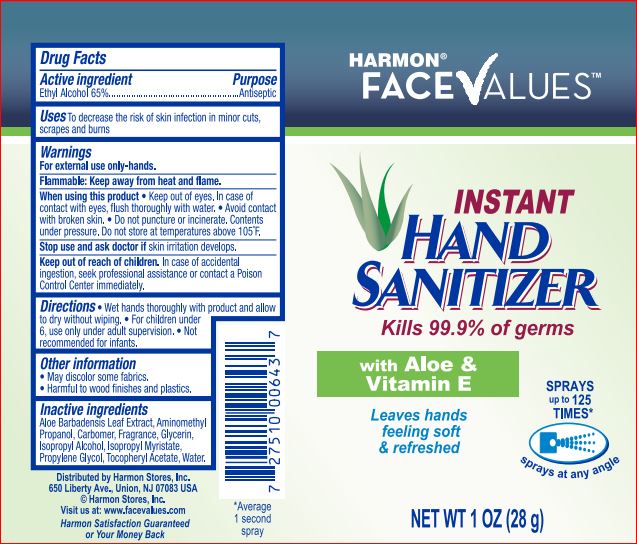 DRUG LABEL: Instant Hand Sanitizer
NDC: 63940-111 | Form: LIQUID
Manufacturer: Harmon
Category: otc | Type: HUMAN OTC DRUG LABEL
Date: 20171006

ACTIVE INGREDIENTS: ALCOHOL 65 g/100 g
INACTIVE INGREDIENTS: ALOE VERA LEAF; AMINOMETHYLPROPANOL; CARBOMER 934; Glycerin; Isopropyl Alcohol; Isopropyl Myristate; Propylene Glycol; .ALPHA.-TOCOPHEROL ACETATE; Water

Drug Facts

Active ingredients Purpose

Ethyl Alcohol 65.00% Antiseptoc

Keep out of reach of children. If product is swallowed, get medical help or contact a Poison Control Center right away

Uses

To decrease the risk of skin infection in minor cuts, scrapes and burns

Directions
Wet hands thoroughly with product and allow to dry without wiping. For children under 6, use only under adult supervision. Not recommended for infants.

Inactive ingredients

Aloe Barbadensis Leaf Extract
Aminomethyl Propanol
Carbomer
Fragrance
Glycerin
Isopropyl Alcohol
Isopropyl Myristate
Propylene Glycol
Tocopheryl Acetate
Water